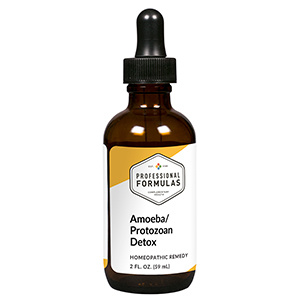 DRUG LABEL: Amoeba/Protozoan Detox
NDC: 63083-6046 | Form: LIQUID
Manufacturer: Professional Complementary Health Formulas
Category: homeopathic | Type: HUMAN OTC DRUG LABEL
Date: 20190815

ACTIVE INGREDIENTS: CHELIDONIUM MAJUS WHOLE 3 [hp_X]/59 mL; ARTEMISIA CINA PRE-FLOWERING TOP 3 [hp_X]/59 mL; EUCALYPTUS GLOBULUS LEAF 3 [hp_X]/59 mL; DRYOPTERIS FILIX-MAS ROOT 4 [hp_X]/59 mL; GARLIC 6 [hp_X]/59 mL; ANTIMONY POTASSIUM TARTRATE 6 [hp_X]/59 mL; WORMWOOD 6 [hp_X]/59 mL; TARAXACUM OFFICINALE FLOWERING TOP 6 [hp_X]/59 mL; BOS TAURUS LARGE INTESTINE 6 [hp_X]/59 mL; IPECAC 6 [hp_X]/59 mL; BEEF LIVER 6 [hp_X]/59 mL; BEEF LUNG 6 [hp_X]/59 mL; SPIGELIA MARILANDICA ROOT 6 [hp_X]/59 mL; AMMONIUM CATION 6 [hp_X]/59 mL; ARSENIC TRIOXIDE 8 [hp_X]/59 mL; LYTTA VESICATORIA 12 [hp_X]/59 mL; BLASTOCYSTIS HOMINIS 30 [hp_X]/59 mL; CRYPTOSPORIDIUM HOMINIS 30 [hp_X]/59 mL; DIENTAMOEBA FRAGILIS 30 [hp_X]/59 mL; ENTAMOEBA HISTOLYTICA 30 [hp_X]/59 mL; GIARDIA LAMBLIA 30 [hp_X]/59 mL; PLASMODIUM KNOWLESI 30 [hp_X]/59 mL; TOXOPLASMA GONDII 30 [hp_X]/59 mL; TRICHOMONAS VAGINALIS 30 [hp_X]/59 mL
INACTIVE INGREDIENTS: ALCOHOL; WATER

X46

ACTIVE INGREDIENTS

Chelidonium majus 3X
Cina 3X
Eucalyptus globulus 3X
Filix mas 4X
Allium sativum 6X
Antimonium tartaricum 6X
Artemisia absinthium 6X
Herbal bitters 6X
Intestines (small and large) 6X
Ipecacuanha 6X
Liver 6X
Lung 6X
Spigelia marilandica 6X
Ammonium phosphoricum 6X, 12X
Arsenicum album 8X
Cantharis 12X
and all the following at 30X, 60X, 100X:
Blastocystis hominis
Cryptosporidium
Dientamoeba fragilis
Endolimax nana
Entamoeba histolytica
Giardia lamblia
Plasmodium
Toxoplasmosis
Trichomonas vaginalis

QUESTIONS

Professional Formulas

PO Box 2034 Lake Oswego, OR 97035

INDICATIONS

For the temporary relief of mild abdominal pain, diarrhea, bloating, nausea or vomiting, indigestion, occasional headache, muscle aches or pains, fatigue, or feelings of discomfort or uneasiness.*

PURPOSE

*Claims based on traditional homeopathic practice, not accepted medical evidence. Not FDA evaluated.

WARNINGS

Persistent symptoms may be a sign of a serious condition. If symptoms persist or are accompanied by a fever, rash, or persistent headache, consult a doctor. Keep out of the reach of children. In case of overdose, get medical help or contact a poison control center right away. If pregnant or breastfeeding, ask a healthcare professional before use.

Keep out of the reach of children.

PREGNANCY OR BREAST FEEDING

If pregnant or breastfeeding, ask a healthcare professional before use.

DIRECTIONS

Place drops under tongue 30 minutes before/after meals. Adults and children 12 years and over: Take 10 drops up to 3 times per day. Consult a physician for use in children under 12 years of age.

OTHER INFORMATION

Tamper resistant. If seal is broken, do not use. After opening, close container tightly and store at room temperature away from heat.

INACTIVE INGREDIENTS

20% ethanol, purified water.

LABEL

Est 1985

Professional Formulas

Complementary Health

Amoeba/Protozoan Detox

Homeopathic Remedy

2 FL. OZ. (59 mL)